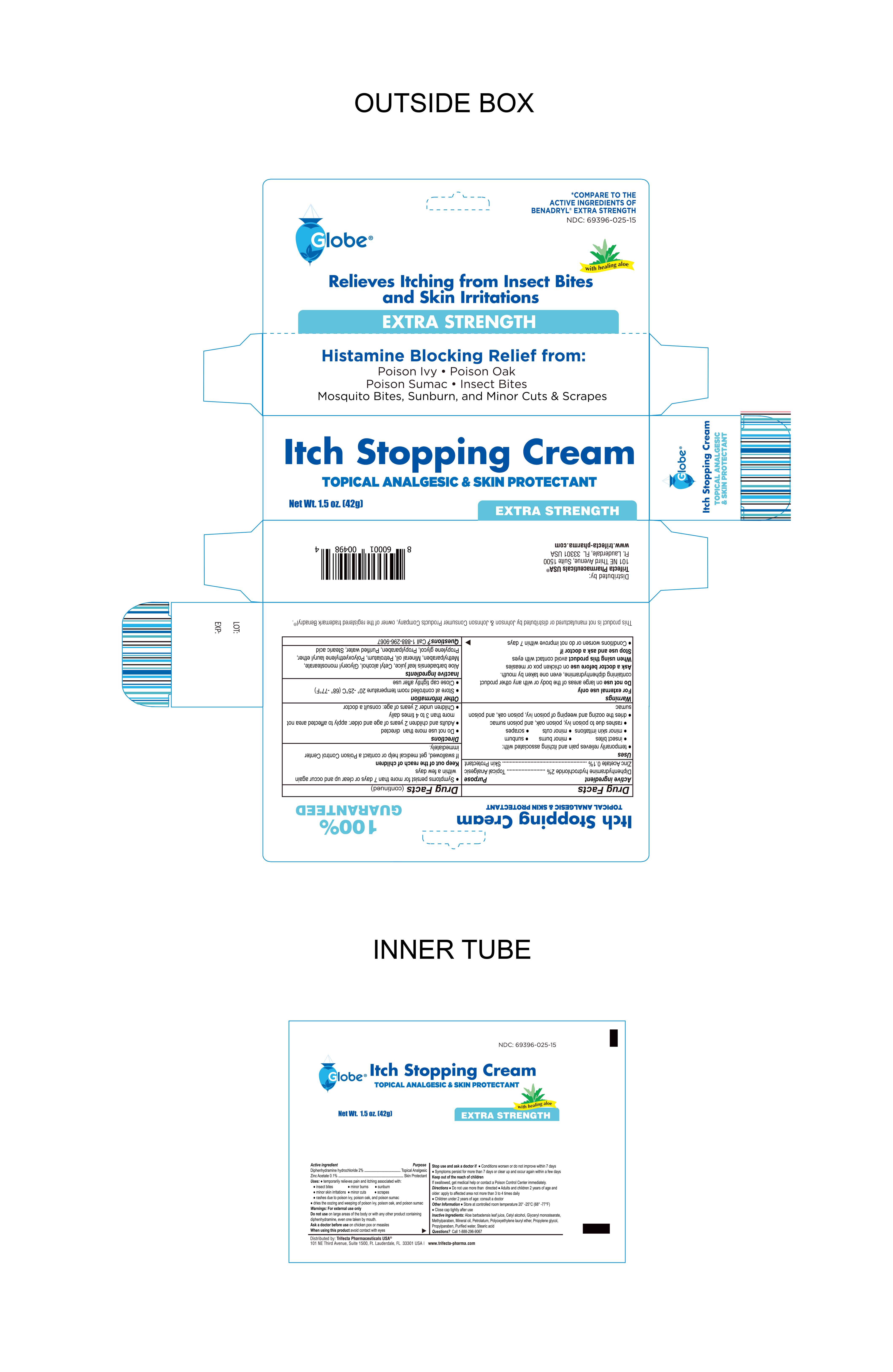 DRUG LABEL: Anti-Itch Cream
NDC: 69396-025 | Form: CREAM
Manufacturer: Trifecta Pharmaceuticals USA, LLC.
Category: otc | Type: HUMAN OTC DRUG LABEL
Date: 20240102

ACTIVE INGREDIENTS: DIPHENHYDRAMINE HYDROCHLORIDE 2 g/100 g; ZINC ACETATE 0.1 g/100 g
INACTIVE INGREDIENTS: LAURETH-23; WATER; CETOSTEARYL ALCOHOL; PETROLATUM; MINERAL OIL; STEARYL ALCOHOL; METHYLPARABEN; PROPYLENE GLYCOL; STEARIC ACID; GLYCERYL MONOSTEARATE; PROPYLPARABEN

Anti-Itch Cream

Active Ingredient

Diphenhydramine Hydrochloride 2%

Purpose

Topical Analgesic

Active Ingredient

Zinc Acetate 0.1%

Purpose

Skin Protectant

INDICATIONS AND USAGE

For the temporary relief from pain and itching associated with

- insect bites
- minor burns
- minor skin irritation
- rashes due to poison ivy, poison oak, and poison sumac
- dries the weeping and oozing of poison ivy, oak and sumac

Warnings

For External Use Only

Do not use on large areas of the body or with any other product containing diphenhydramine, even one taken by mouth

Ask a doctor before use on chicken pox or measles

When using this product avoid contact with eyes

Stop use and ask a doctor if

- Conditions worsen or do not improve within 7 days
- Symptoms persist for more than 7 days or clear up and occur again within a few days

Stop use and ask a doctor

- Conditions worsen or do not improve within 7 days
- Symptoms persist for more than 7 days or clear up and occur again within a few days

Keep out of the reach of children

If swallowed, get medical help or contact a Poison Control Center immediately

Directions

- Do not use more than directed
- Adults and children 2 years of age and older: apply to affected area not more than 3 to 4 times daily
- Children under 2 years of age: consult a doctor

Other information

- Store at controlled room temperature 20º-25ºC (68º-77ºF)
- Close cap tightly after use

Questions? Call 1-888-296-9067

Inactive Ingredients

Aloe Vera (Aloe Barbadensis) leaf juice, Cetyl alcohol, Glyceryl monostearate, Methylparaben, Mineral Oil, Petrolatum, Polyoxyethylene lauryl ether, Propylene glycol, Propylparaben, Purified Water, Stearic acid

Distributed By:

Trifecta Pharmaceuticals USA, LLC.

101 NE Third Avenue, Suite 1500

Ft. Lauderdale, FL. 33301 USA

Product of PRC

www.trifecta-pharma.com